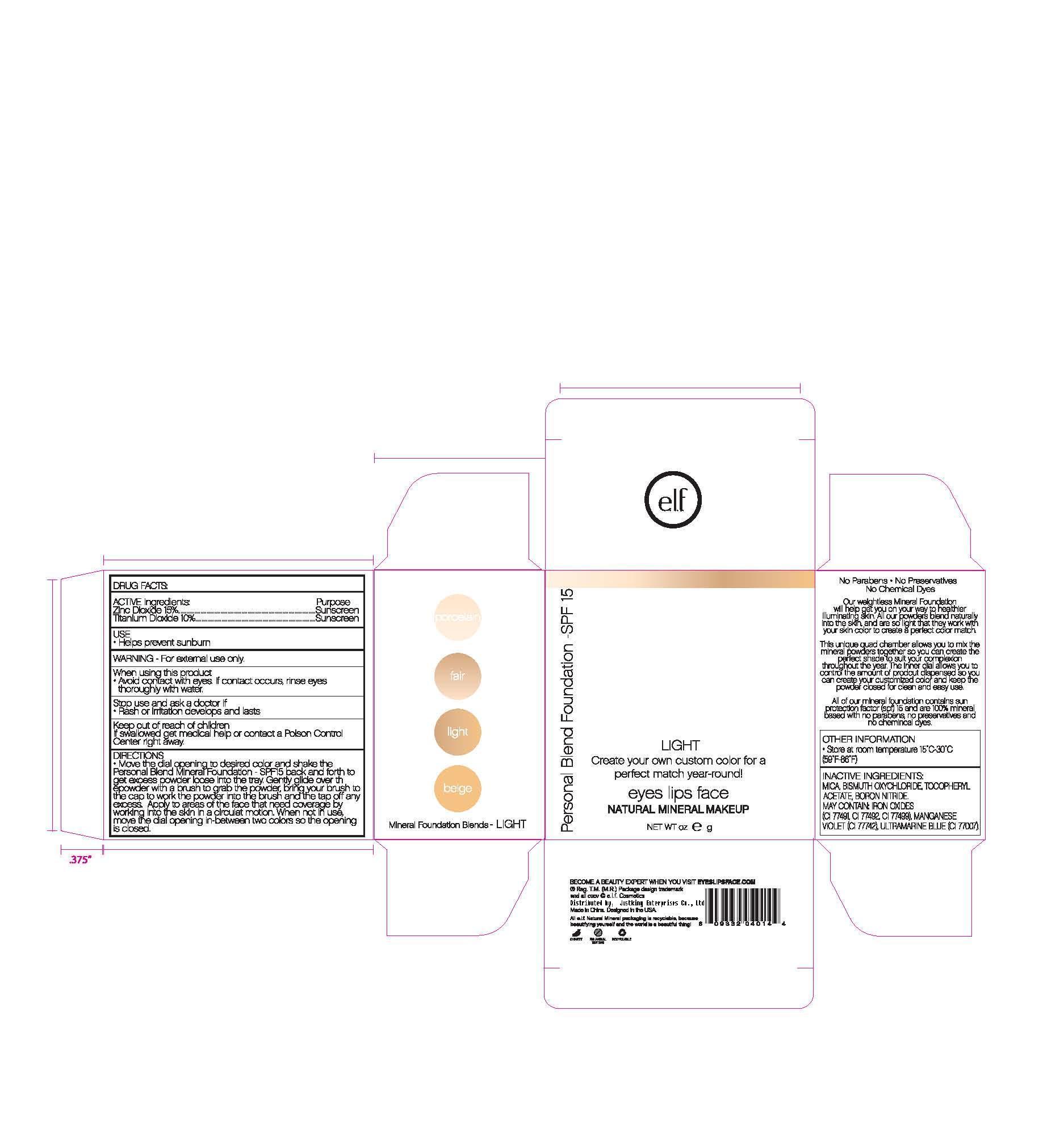 DRUG LABEL: ELF Personal Blend Foundation SPF 15
NDC: 76166-001 | Form: POWDER
Manufacturer: Shanghai Justking Enterprise Co. Ltd.
Category: otc | Type: HUMAN OTC DRUG LABEL
Date: 20110501

ACTIVE INGREDIENTS: TITANIUM DIOXIDE 10 g/100 g; ZINC OXIDE 15 g/100 g
INACTIVE INGREDIENTS: BISMUTH OXYCHLORIDE; .ALPHA.-TOCOPHEROL ACETATE, DL-; MICA; FERRIC OXIDE RED; FERRIC OXIDE YELLOW; FERROSOFERRIC OXIDE

Drug Fact

Active Ingredient:

Zinc Oxide: 15%

Titanium Dioxide: 10%

Purpose:

Sunscreen

Uses:

Help prevent Sunburn

Warning:

For external use only

When Using This Product:

Avoid contact with eyes. If contact occurs, rinse thoroughly with water

Stop Use and Ask a Doctor if:

Rash or irritation develops and lasts

Keep Out of Reach of Children:

If swallowed get medical help or contact a Poison Control Center immediately

Directions:

Move the dial opening to desired color and shake the Personal Blend Foundation SPF 15 back and forth to get excess powder loose onto the tray. Gently glide over the powder with a brush to grab the powder, bring your brush to the cap to work in the powder to the brush, then tap off any excess. Apply to the areas of the face that need coverage by working into the skin in a circular motion. When not in use, move the dial opening in between two colors so the dial opening is closed.

STORAGE AND HANDLING

Other Imformation:

Store at room temperature 15-30C (59-86F)

Inactive Ingredient:

Mica, Fragrance, Bismuth Oxychloride, Tocopheryl Acetate, Boron Nitride

May contain:

Iron Oxides (CI 77491, CI 77492, CI 77499), Manganese Violet (CI 77742), Ultramarine Blue (CI 77007)

label